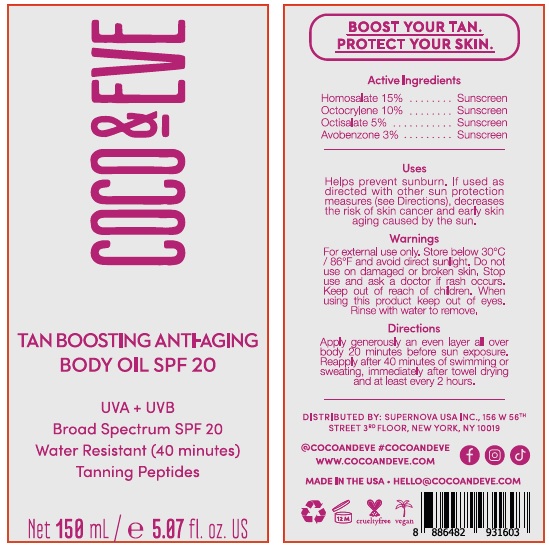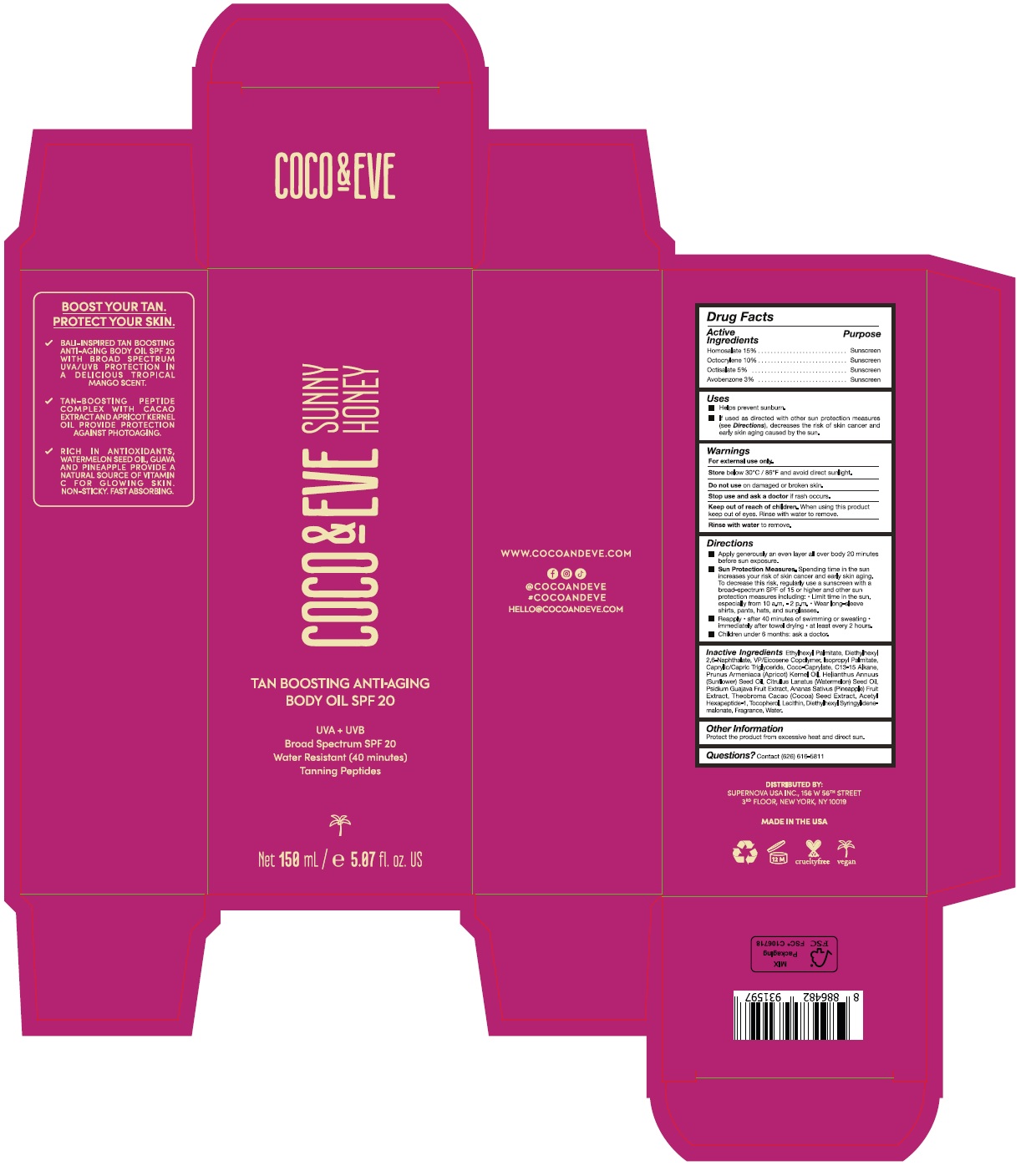 DRUG LABEL: coco and eve tan boosting anti-aging body oil spf 20
NDC: 82931-012 | Form: LOTION
Manufacturer: Supernova USA Inc.
Category: otc | Type: HUMAN OTC DRUG LABEL
Date: 20240528

ACTIVE INGREDIENTS: HOMOSALATE 15 g/100 mL; OCTOCRYLENE 10 g/100 mL; OCTISALATE 5 g/100 mL; AVOBENZONE 3 g/100 mL
INACTIVE INGREDIENTS: ETHYLHEXYL PALMITATE; DIETHYLHEXYL 2,6-NAPHTHALATE; VINYLPYRROLIDONE/EICOSENE COPOLYMER; ISOPROPYL PALMITATE; MEDIUM-CHAIN TRIGLYCERIDES; COCO-CAPRYLATE; C13-15 ALKANE; APRICOT KERNEL OIL; SUNFLOWER OIL; WATERMELON SEED OIL; GUAVA; PINEAPPLE; COCOA; ACETYL HEXAPEPTIDE-1; TOCOPHEROL; LECITHIN, SOYBEAN; DIETHYLHEXYL SYRINGYLIDENEMALONATE; ETHYL VANILLIN; VANILLIN; OCTAHYDROCOUMARIN; PIPERONAL; ETHYL MALTOL; SANDALORE; HEXYL SALICYLATE; 6,6-DIMETHOXY-2,5,5-TRIMETHYL-2-HEXENE; ETHYL LINALOOL; ISOCYCLEMONE E; BUTYLATED HYDROXYTOLUENE; .DELTA.-DAMASCONE; HEXAMETHYLINDANOPYRAN; .BETA.-DAMASCENONE; METHYL 2-NONYNOATE; WATER

COCO & EVE TAN BOOSTING ANTI AGING BODY OIL SPF 20

Drug Facts

Active Ingredients
Homosalate 15%
Octocrylene 10%
Octisalate 5%
Avobenzone 3%

Purpose
Sunscreen
Sunscreen
Sunscreen
Sunscreen

Uses

- Helps prevent sunburn.
- If used as directed with other sun protection measures (see Directions), decreases the risk of skin cancer and early skin aging caused by the sun.

Warnings

For external use only.

Store below 30°C / 86°F and avoid direct sunlight.

Do not use on damaged or broken skin.

Stop use and ask a doctor if rash occurs.

Keep out of reach of children. When using this product keep out of eyes. Rinse with water to remove.

Rinse with water to remove.

Directions

- Apply generously an even layer all over body 20 minutes before sun exposure.
- Sun Protection Measures. Spending time in the sun increases your risk of skin cancer and early skin aging. To decrease this risk, regularly use a sunscreen with a broad-spectrum SPF of 15 or higher and other sun protection measures including:
  - Limit time in the sun, especially from 10 a.m. - 2 p.m.
  - Wear long-sleeve shirts, pants, hats, and sunglasses.
- Reapply
  - after 40 minutes of swimming or sweating
  - immediately after towel drying
  - at least every 2 hours.
- Children under 6 months: ask a doctor.

INACTIVE INGREDIENT

Inactive Ingredients Ethylhexyl Palmitate, Diethylhexyl 2,6-Naphthalate, VP/Eicosene Copolymer, Isopropyl Palmitate, Caprylic/Capric Triglyceride, Coco-Caprylate, C13-15 Alkane, Prunus Armeniaca (Apricot) Kernel Oil, Helianthus Annuus (Sunflower) Seed Oil, Citrullus Lanatus (Watermelon) Seed Oil, Psidium Guajava Fruit Extract, Ananas Sativus (Pineapple) Fruit Extract, Theobroma Cacao (Cocoa) Seed Extract, Acetyl Hexapeptide-1, Tocopherol, Lecithin, Diethylhexyl Syringylidenemalonate, Fragrance, Water.

Other Information

Protect the product from excessive heat and direct sun.

Questions? Contact (626) 616-5811

PRINCIPAL DISPLAY PANEL

COCO & EVE

TAN BOOSTING ANTI-AGING
BODY OIL SPF 20

UVA + UVB

Broad Spectrum SPF 20

Water Resistant (40 minutes)

Tanning Peptides

Net 150 mL / e 5.07 fl. oz. US

COCO & EVE

SUNNY
HONEY

TAN BOOSTING ANTI-AGING
BODY OIL SPF 20

UVA + UVB

Broad Spectrum SPF 20

Water Resistant (40 minutes)

Tanning Peptides

Net 150 mL / e 5.07 fl. oz. US